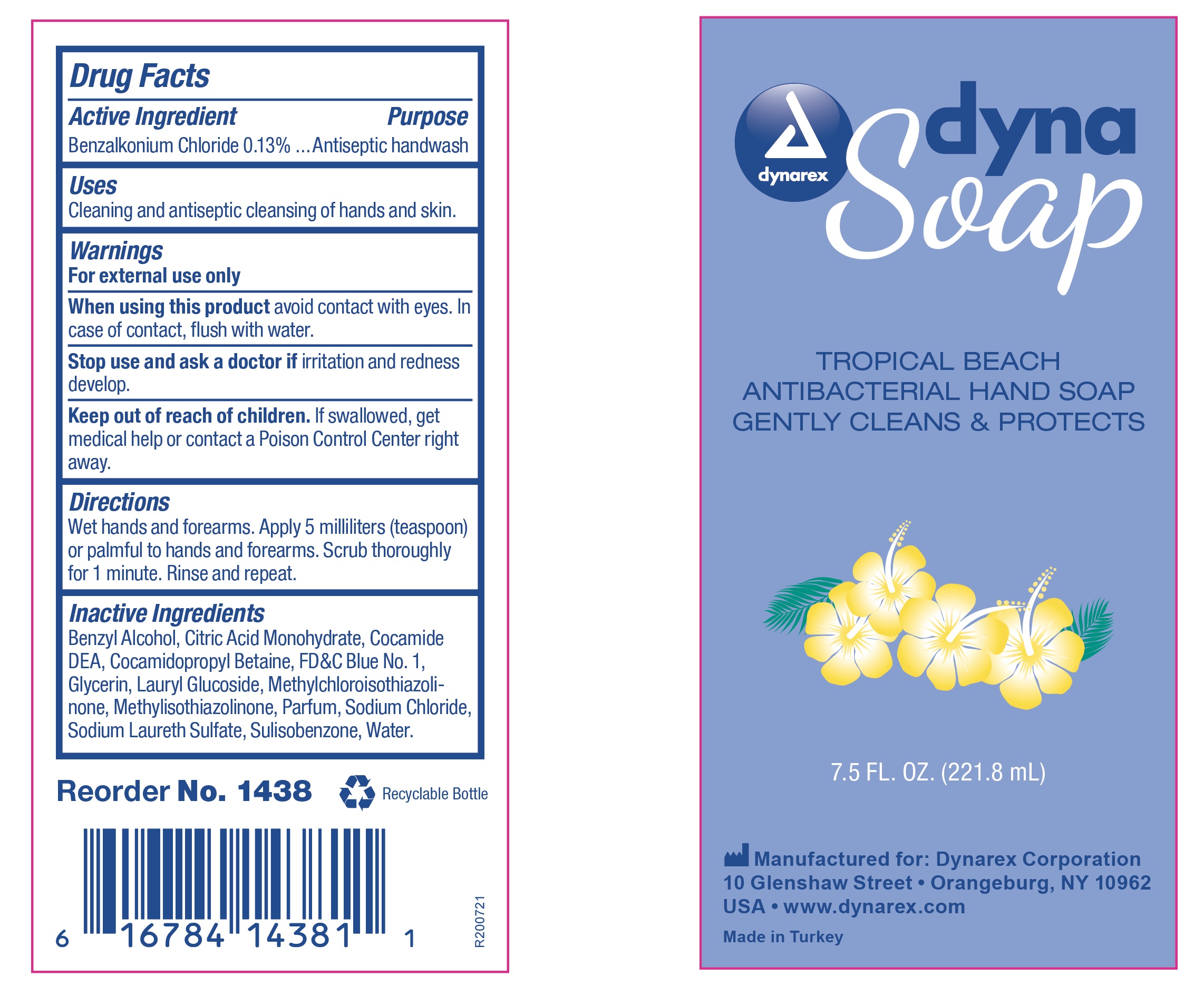 DRUG LABEL: 1438 DynaSoap
NDC: 67777-319 | Form: SOAP
Manufacturer: Dynarex Corporation
Category: otc | Type: HUMAN OTC DRUG LABEL
Date: 20241120

ACTIVE INGREDIENTS: BENZALKONIUM CHLORIDE 0.13 g/100 g
INACTIVE INGREDIENTS: SULISOBENZONE; SODIUM LAURETH SULFATE; LAURYL GLUCOSIDE; METHYLCHLOROISOTHIAZOLINONE; COCAMIDOPROPYL BETAINE; GLYCERIN; METHYLISOTHIAZOLINONE; COCO DIETHANOLAMIDE; SODIUM CHLORIDE; CITRIC ACID MONOHYDRATE; WATER; BENZYL ALCOHOL; FD&C BLUE NO. 1

1438 Dyna Soap - Antibacterial Hand Soap 67777-319-01

Active Ingredient

Benzalkonium Chloride 0.13%.......Antiseptic handwash

Purpose

Antibacterial Hand Soap

Use

Cleaning and antiseptic cleansing of hands and skin.

Warnings

For external use only.

When using this product

Avoid contact with eyes. In case of contact, flush with water.

Stop use and ask a doctor if.

Irritation and redness develop.

Keep out of reach of children.

If swallowed, get medical help or contact a Poison Control Center right away.

Directions.

Wet hands and forearms. Apply 5 millileters (teaspoon) or palmful to hands and forearms. Scrub thoroughly for 1 minute. Rinse and repeat.

Inactive Ingredients

Benzyl Alcohol, Citric Acid Monohydrate, Cocamide DEA, Cocamidopropyl Betaine, Glycerin, Lauryl Glucoside, Methylchloroisothiazolinone, Methylisothiazolinone, Parfum, Sodium Chloride, Sodium Laureth Sulfate, Sulisobenzone, Water.

Label

1438 DynaSoap Label